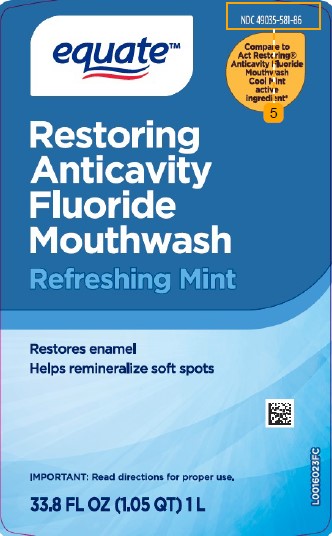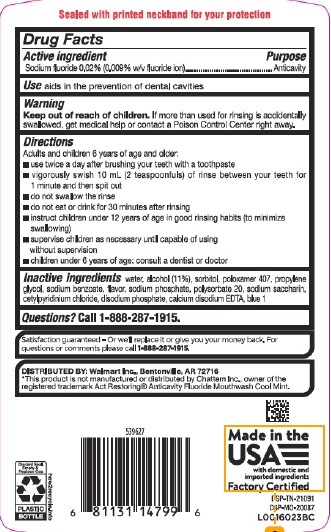 DRUG LABEL: Anticavity
NDC: 49035-581 | Form: MOUTHWASH
Manufacturer: Walmart Inc.
Category: otc | Type: HUMAN OTC DRUG LABEL
Date: 20260227

ACTIVE INGREDIENTS: SODIUM FLUORIDE 0.2 mg/1 mL
INACTIVE INGREDIENTS: WATER; ALCOHOL; SORBITOL; POLOXAMER 407; PROPYLENE GLYCOL; SODIUM BENZOATE; SODIUM PHOSPHATE; POLYSORBATE 20; SACCHARIN SODIUM; CETYLPYRIDINIUM CHLORIDE; SODIUM PHOSPHATE, DIBASIC, ANHYDROUS; EDETATE CALCIUM DISODIUM ANHYDROUS; FD&C BLUE NO. 1

Equate 581.000/581AA-AC
Restoring Anticavity Fluoride Mouthwash

Tamper Evident Statement

Sealed with printed neckband for your protection

Active ingredient

Sodium fluoride 0.02% (0.009% w/v fluoride ion)

Purpose

Anticavity

Use

aids in the prevention of dental cavities

Warning

For this product

Keep out of reach of children.

If more than used for rinsing is accidentally swallowed, get medical help or contact a Poison Control Center right away.

Directions

Adults and children 6 years of age and older:

- use twice a day after brushing your teeth with a toothpaste
- vigorously swish 10 mL (2 teaspoonfuls) of rinse between your teeth for 1 minute and then spit out
- do not swallow the rinse
- do not eat or drink for 30 minutes after rinsing
- instruct children under 12 years of age in good rinsing habits (to minimize swallowing)
- supervise children as necessary until capable of using without supervision
- children under 6 years of age: consult a dentist or doctor

Inactive ingredients

water, alcohol (11%), sorbitol, poloxamer 407, propylene glycol, sodium benzoate, flavor, sodium phosphate, polysorbate 20, sodium saccharin, cetylpyridinium chloride, disodium phosphate calcium disodium EDTA, blue 1

Questions?

Call 1-888-287-1915

Adverse reaction

Satisfaction guaranteed - Or we'll replace it or give you your money back. For questions or comments please call 1-888-287-1915.

DISTRIBUTED BY: Walmart, Inc., Bentonville, AR 72716

Discard Seal, Empty & Replace Cap

PLASTIC BOTTLE

how2recycle.info

Made in the USA

with domestic and imported ingredients

Factory Certified

DSP-TN-21091

DSP-MO-20087

Disclaimer

*This product is not manufactured or distributed by Chattem Inc., owner of the registered trademark Act Restoring® Anticavity Fluoride Mouthwash Cool Mint.

Principal panel display

equate™

NDC 49035-581-86

Compare to Act Restoring®Anticavity Fluoride Mouthwash Coll Mint active ingredient*

Restoring Anticavity Fluoride Mouthwash

Refreshing Mint

Restores enamel

Helps remineralize soft spots

IMPORTANT: read directions for proper use.

33.8 FL OZ (1.05 QT) 1 L